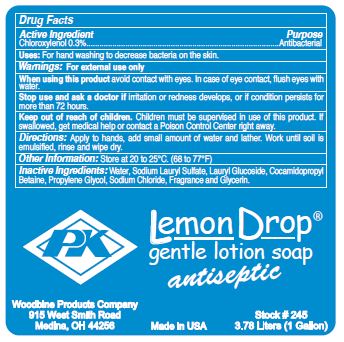 DRUG LABEL: Lemon Drop Gentle Antiseptic
NDC: 11429-1006 | Form: LIQUID
Manufacturer: Woodbine Products Company
Category: otc | Type: HUMAN OTC DRUG LABEL
Date: 20250617

ACTIVE INGREDIENTS: CHLOROXYLENOL 3 mg/1 mL
INACTIVE INGREDIENTS: WATER; SODIUM LAURYL SULFATE; LAURYL GLUCOSIDE; COCAMIDOPROPYL BETAINE; PROPYLENE GLYCOL; SODIUM CHLORIDE; GLYCERIN

Drug Facts 11429-1006

Active Ingredient

Choroxylenol 0.3%

Purpose

Antibacterial

Uses:

For hand washing to decrease bacteria on the skin.

Warnings:

For external use only

When using this product avoid contact with eyes.

In case of eye contact, flush eyes with water.

Stop use and ask a doctor if irritation or redness develops, or if condition persists for more than 72 hours.

Keep out of reach of children.

Children must be supervised in use of this product.

If swallowed, get medical help or contact a Poison control Center right away.

Directions:

Apply to hands, add small amount of water and lather.

Work until soil is emulsified, rinse and wipe dry.

Other Information:

Store at 20 to 25 C (68 to 77 F)

Inactive Ingredients:

Water, Sodium Lauryl Sulfate, Lauryl Glucoside, Cocamidopropyl Betaine, Propylene Glycol, Sodium Chloride, Fragrance and Glycerin.

PACKAGE LABEL

PK

Lemon Drop

gentle lotion soap

antiseptic

Woodbine Products Company

915 West Smith Road

Medina, OH 44256

Made in USA

Stock # 245

3.78 Liters (1 Gallon)